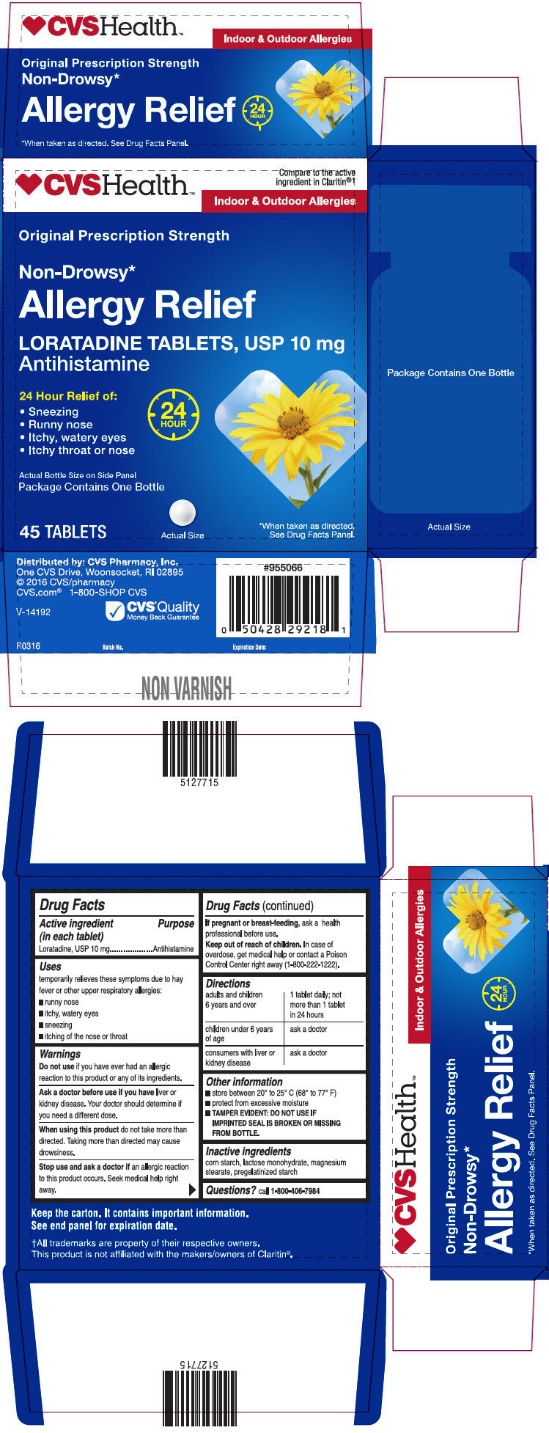 DRUG LABEL: Loratadine
NDC: 59779-528 | Form: TABLET
Manufacturer: CVS Pharmacy
Category: otc | Type: HUMAN OTC DRUG LABEL
Date: 20211221

ACTIVE INGREDIENTS: LORATADINE 10 mg/1 1
INACTIVE INGREDIENTS: STARCH, CORN; LACTOSE MONOHYDRATE; MAGNESIUM STEARATE

Drug Facts

ACTIVE INGREDIENT (IN EACH TABLET)

Loratadine, USP 10 mg

PURPOSE

Antihistamine

USES

Temporarily relieves these symptoms due to hay fever or other upper respiratory allergies:

- runny nose
- itchy, watery eyes
- sneezing
- itching of the nose or throat

WARNINGS

Do not use

If you have ever had an allergic reaction to this product or any of its ingredients.

Ask a doctor before use if you have

Liver or kidney disease. Your doctor should determine if you need a different dose.

When using this product

Do not take more than directed. Taking more than directed may cause drowsiness.

Stop use and ask a doctor if

An allergic reaction to this product occurs. Seek medical help right away.

If pregnant or breast-feeding,

Ask a health professional before use.

Keep out of reach of children.

In case of overdose, get medical help or contact a Poison Control Center right away (1-800-222-1222).

DIRECTIONS

adults and children 6 years and over | 1 tablet daily; not more than 1 tablet in 24 hours
children under 6 years of age | ask a doctor
consumers with liver or kidney disease | ask a doctor

OTHER INFORMATION

- store between 20° to 25° C (68° to 77° F)
- protect from excessive moisture
- TAMPER EVIDENT: DO NOT USE IF IMPRINTED SEAL IS BROKEN OR MISSING FROM BOTTLE.

INACTIVE INGREDIENTS

Corn starch, lactose monohydrate, magnesium stearate, pregelatinized starch

QUESTIONS?

Call 1-800-406-7984

PRINCIPAL DISPLAY PANEL - 10 mg Tablet Bottle Carton

CVSHealth™

Compare to the active
ingredient in Claritin®†

Indoor & Outdoor Allergies

Original Prescription Strength

Non-Drowsy*

Allergy Relief

LORATADINE TABLETS, USP 10 mg
Antihistamine

24 Hour Relief of:

1. Sneezing
2. Runny nose
3. Itchy, watery eyes
4. Itchy throat or nose

24
HOUR

Actual Bottle Size on Side Panel
Package Contains One Bottle

45 TABLETS

Actual Size

*When taken as directed.
See Drug Facts Panel.